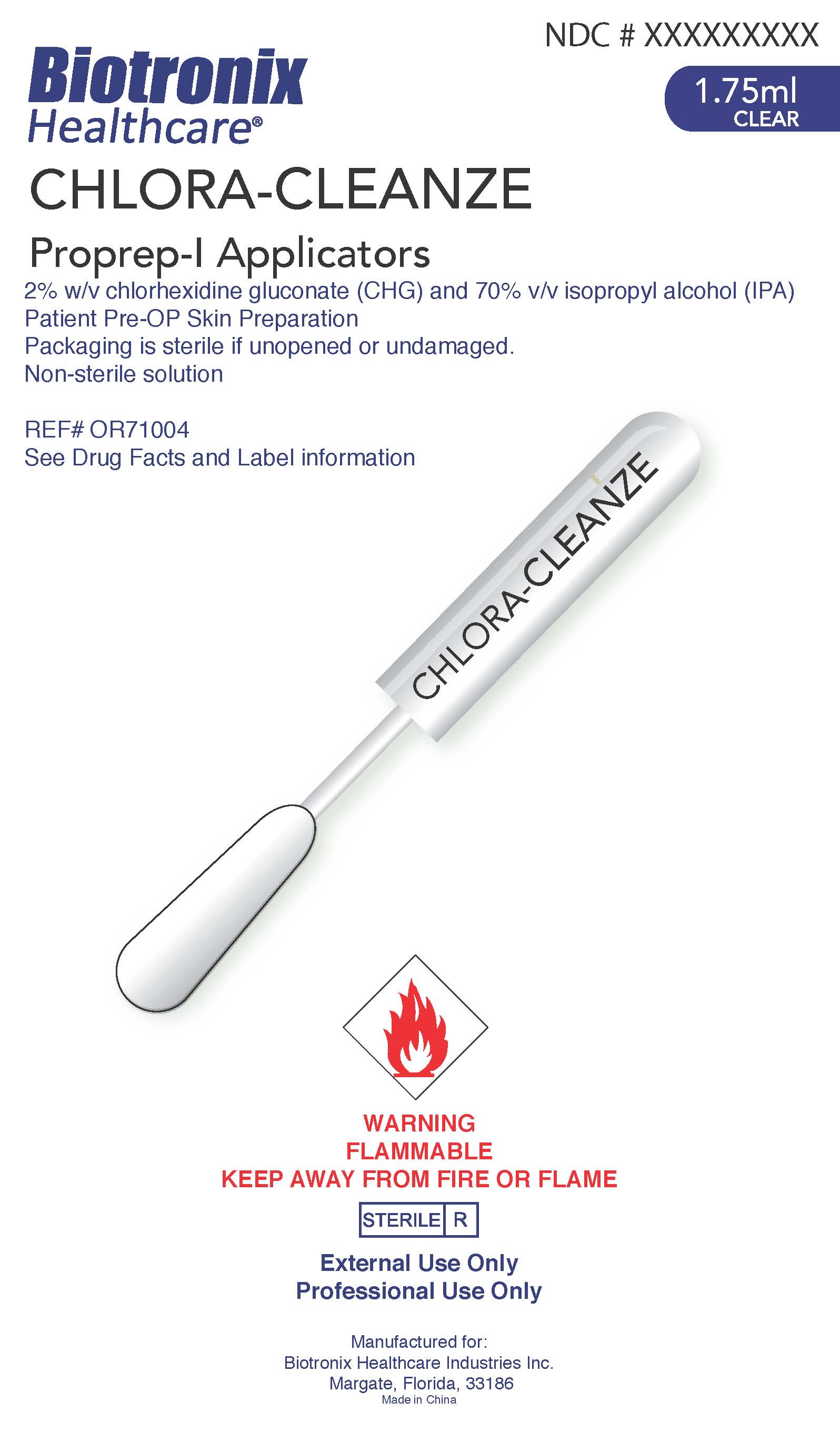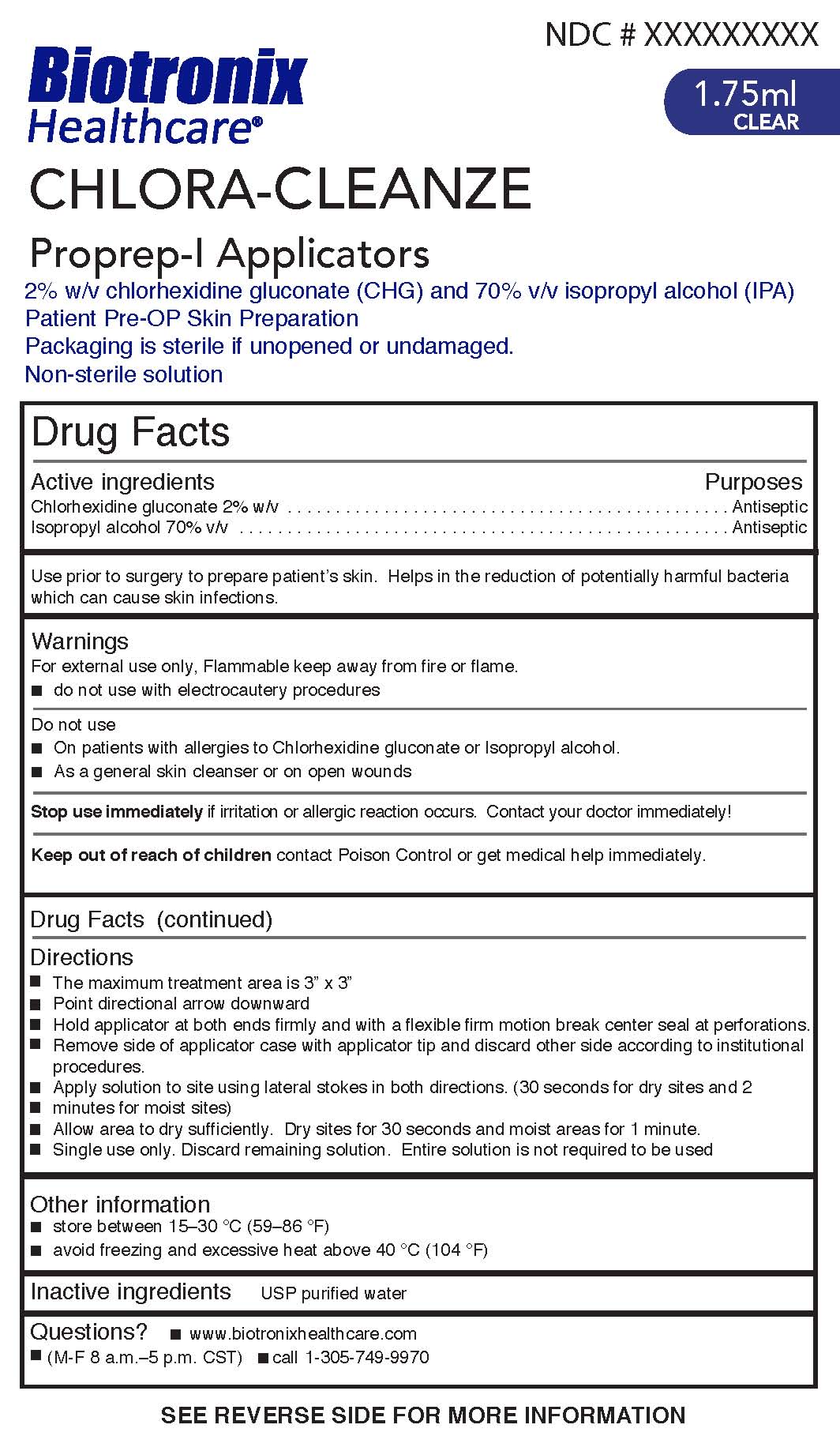 DRUG LABEL: CHLORA-CLEANZE
NDC: 71389-001 | Form: SWAB
Manufacturer: Biotronix Healthcare Industries, Inc.
Category: otc | Type: HUMAN OTC DRUG LABEL
Date: 20170714

ACTIVE INGREDIENTS: CHLORHEXIDINE GLUCONATE 20 mg/1 mL; ISOPROPYL ALCOHOL 0.7 mL/1 mL
INACTIVE INGREDIENTS: WATER

Active ingredients

Chlorhexidine gluconate 2% w/v

Isopropyl alcohol 70% v/v

Purposes
Antiseptic

Warnings
For external use only. Flammable keep away from fire or flame.

- do not use with electrocautery procedures

Do not use

- On patients with allergies to Chlorhexidine gluconate or Isopropyl alcohol
- As a general skin cleanser or on open wounds

Stop use immediately if irritation or allergic reaction occurs. Contact your doctor immediately!

Directions

- The maximum treatment area is 2.5” x 2.5”
- Point directional arrow downward
- Hold applicator at both ends firmly and with a flexible firm motion break center seal at perforations.
- Remove side of applicator case with applicator tip and discard other side according to institutional

procedures.

- Apply solution to site using lateral stokes in both directions. (30 seconds for dry sites and 2

minutes for moist sites)

- Allow area to dry sufficiently. Dry sites for 30 seconds and moist areas for 1 minute.
- Single use only. Discard remaining solution. Entire solution is not required to be used

Inactive ingredients USP purified water

INDICATIONS AND USAGE

Use prior to surgery to prepare patient’s skin. Helps in the reduction of potentially harmful bacteria which can cause skin infections.

Other information
■ store between 15–30 °C (59–86 °F)
■ avoid freezing and excessive heat above 40 °C (104 °F)

Keep out of reach of children contact Poison Control or get medical help immediately.